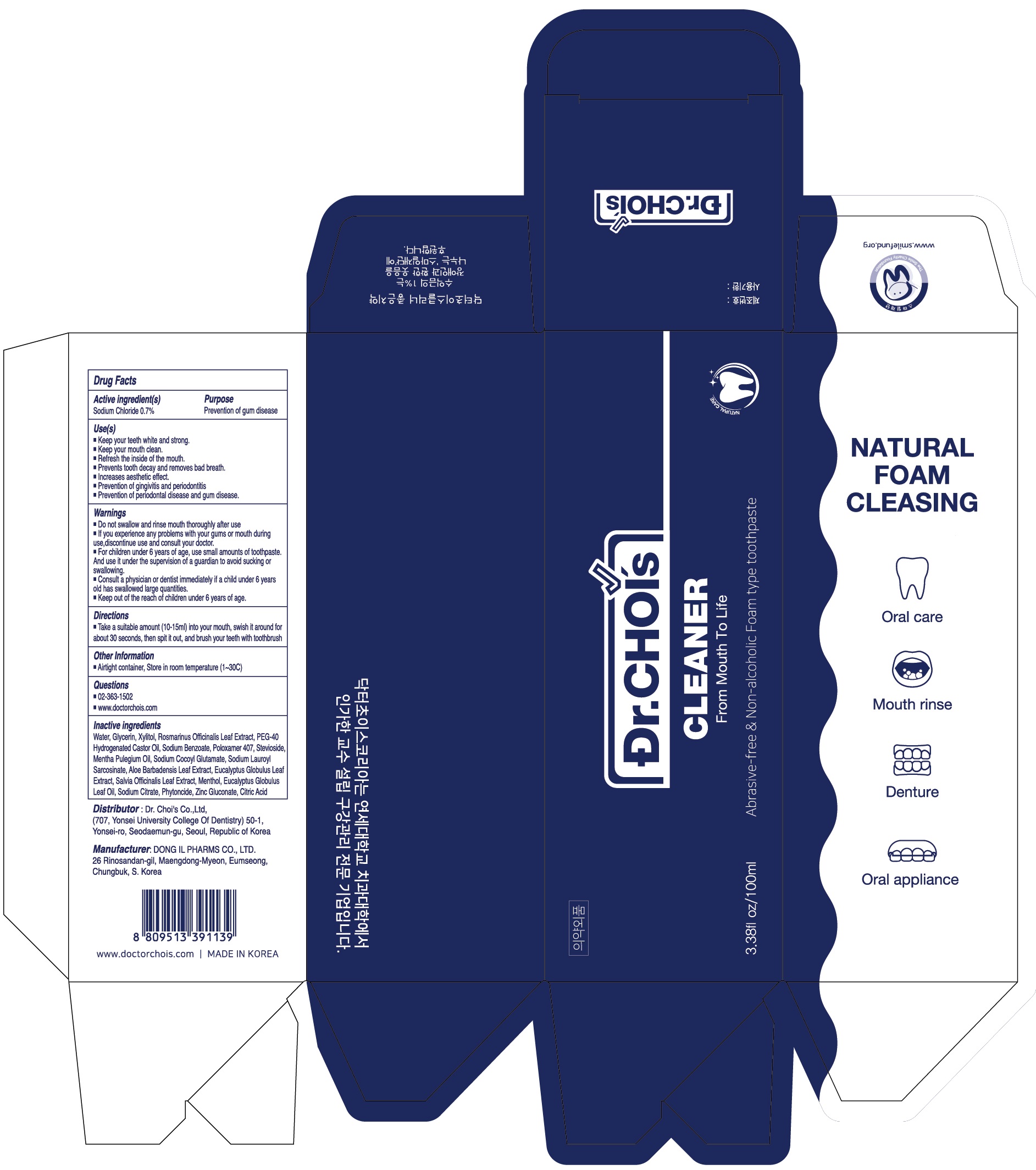 DRUG LABEL: Dr.Chois Cleaner Plus Toothpaste
NDC: 73666-0590 | Form: PASTE, DENTIFRICE
Manufacturer: Doctor Choi`s Korea Co., LTD.
Category: otc | Type: HUMAN OTC DRUG LABEL
Date: 20240416

ACTIVE INGREDIENTS: Sodium Chloride 0.7 g/100 mL
INACTIVE INGREDIENTS: Water; Glycerin; Xylitol

ACTIVE INGREDIENTS

Sodium Chloride 0.7%

PURPOSE

Prevention of gum disease

Uses

■ Keep your teeth white and strong.
■ Keep your mouth clean.
■ Refresh the inside of the mouth.
■ Prevents tooth decay and removes bad breath.
■ Increases aesthetic effect.
■ Prevention of gingivitis and periodontitis
■ Prevention of periodontal disease and gum disease.

WARNINGS

■ Be careful not to swallow, and rinse your mouth thoroughly after use.
■ If an abnormality occurs such as damage to the gums or mouth due to the use of this toothpaste, stop using it and consult a doctor or dentist
■When used by children under the age of 6, use a small amount of toothpaste about the size of a pea per serving, and use under the guidance of a guardian to avoid sucking or swallowing.
■If a child under the age of 6 swallows a large amount, consult a doctor or dentist immediately.
■Keep out of reach of children under the age of 6

KEEP OUT OF REACH OF CHILDREN

■ Keep out of the reach of children under 6 years of age.

Directions

■ Take a suitable amount (10-15ml) into your mouth, swish it around for about 30 seconds, then spit it out, and brush your teeth with toothbrush

Other Information

■ Airtight container, Store in room temperature (1~30C)

Questions

■ 02-363-1502
■ www.doctorchois.com

INACTIVE INGREDIENTS

Water, Glycerin, Xylitol, Rosmarinus Officinalis Leaf Extract, PEG-40 Hydrogenated Castor Oil, Sodium Benzoate, Poloxamer 407, Stevioside, Mentha Pulegium Oil, Sodium Cocoyl Glutamate, Sodium Lauroyl Sarcosinate, Aloe Barbadensis Leaf Extract, Eucalyptus Globulus Leaf Extract, Salvia Officinalis Leaf Extract, Menthol, Eucalyptus Globulus Leaf Oil, Sodium Citrate, Phytoncide, Zinc Gluconate, Citric Acid